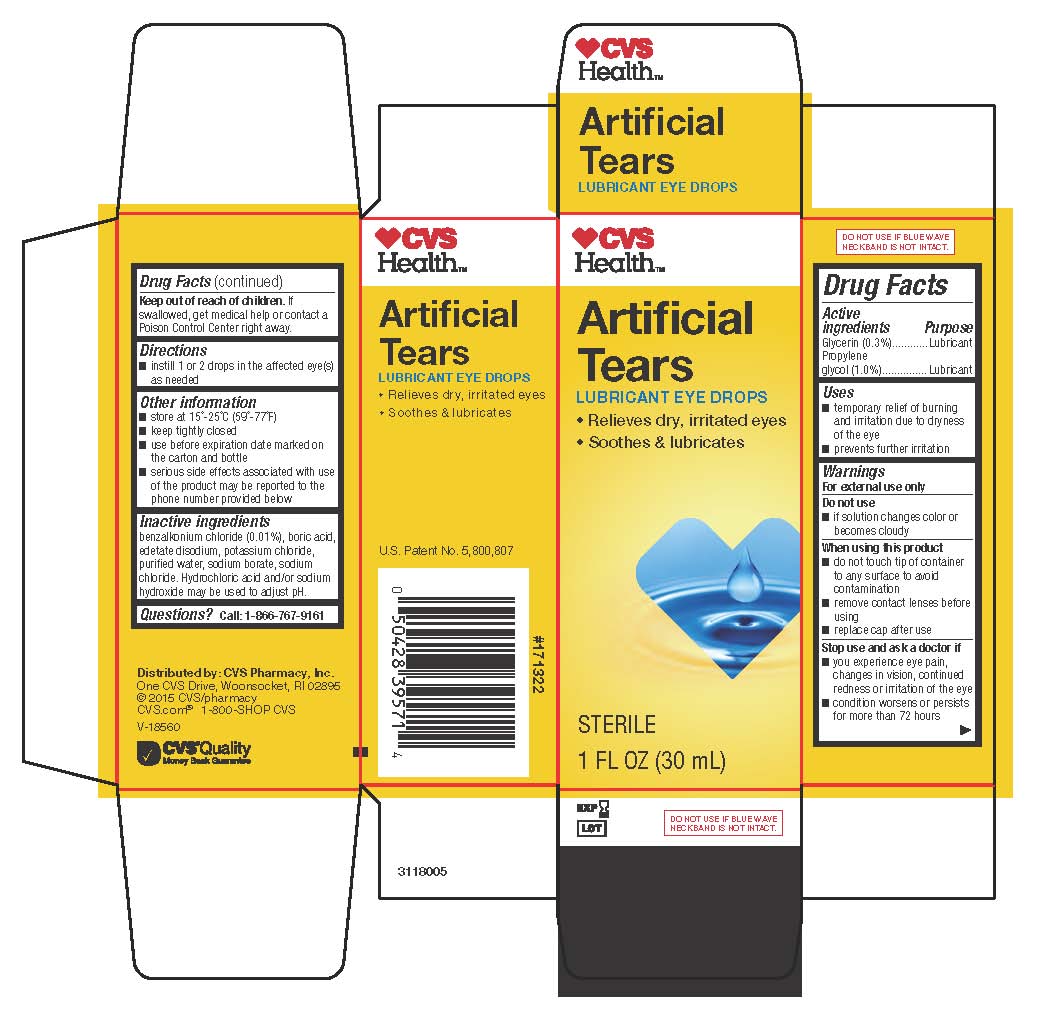 DRUG LABEL: Artificial Tears Lubricant Eye Drops
NDC: 69842-454 | Form: SOLUTION/ DROPS
Manufacturer: CVS Pharmacy
Category: otc | Type: HUMAN OTC DRUG LABEL
Date: 20260206

ACTIVE INGREDIENTS: GLYCERIN 3 mg/1 mL; PROPYLENE GLYCOL 10 mg/1 mL
INACTIVE INGREDIENTS: BENZALKONIUM CHLORIDE; BORIC ACID; EDETATE DISODIUM; POTASSIUM CHLORIDE; WATER; SODIUM BORATE; SODIUM CHLORIDE; HYDROCHLORIC ACID; SODIUM HYDROXIDE

Drug Facts

Active ingredients

Glycerin (0.3%)

Propylene glycol (1.0%)

Purpose

Lubricant

Lubricant

Uses

- temporary relief of burning and irritation due to dryness of the eye
- prevents further irritation

Warnings

For external use only

Do not use

- if solution changes color or becomes cloudy

When using this product

- do not touch tip of container to any surface to avoid contamination
- remove contact lenses before using
- replace cap after use

Stop use and ask a doctor if

- you experience eye pain, changes in vision, continued redness or irritation of the eye
- condition worsens or persists for more than 72 hours

Keep out of reach of children.

If swallowed, get medical help or contact a Poison Control Center right away.

Directions

- instill 1 or 2 drops in the affected eye(s) as needed

Other information

- store at 15°-25°C (59°-77°F)
- keep tightly closed
- use before expiration date marked on the carton and bottle
- serious side effects associated with use of the product may be reported to the phone number provided below

Inactive ingredients

benzalkonium chloride (0.01%), boric acid, edetate disodium, potassium chloride, purified water, sodium borate, sodium chloride. Hydrochloric acid and/or sodium hydroxide may be used to adjust pH.

Questions?

Call: 1-866-767-9161

Package/Label Principal Display Panel

CVS
Health™

Artificial

Tears

LUBRICANT EYE DROPS

- Relieves dry, irritated eyes
- Soothes & lubricates

[icon] blue heart with drop inside

STERILE

1 FL OZ (30 mL)